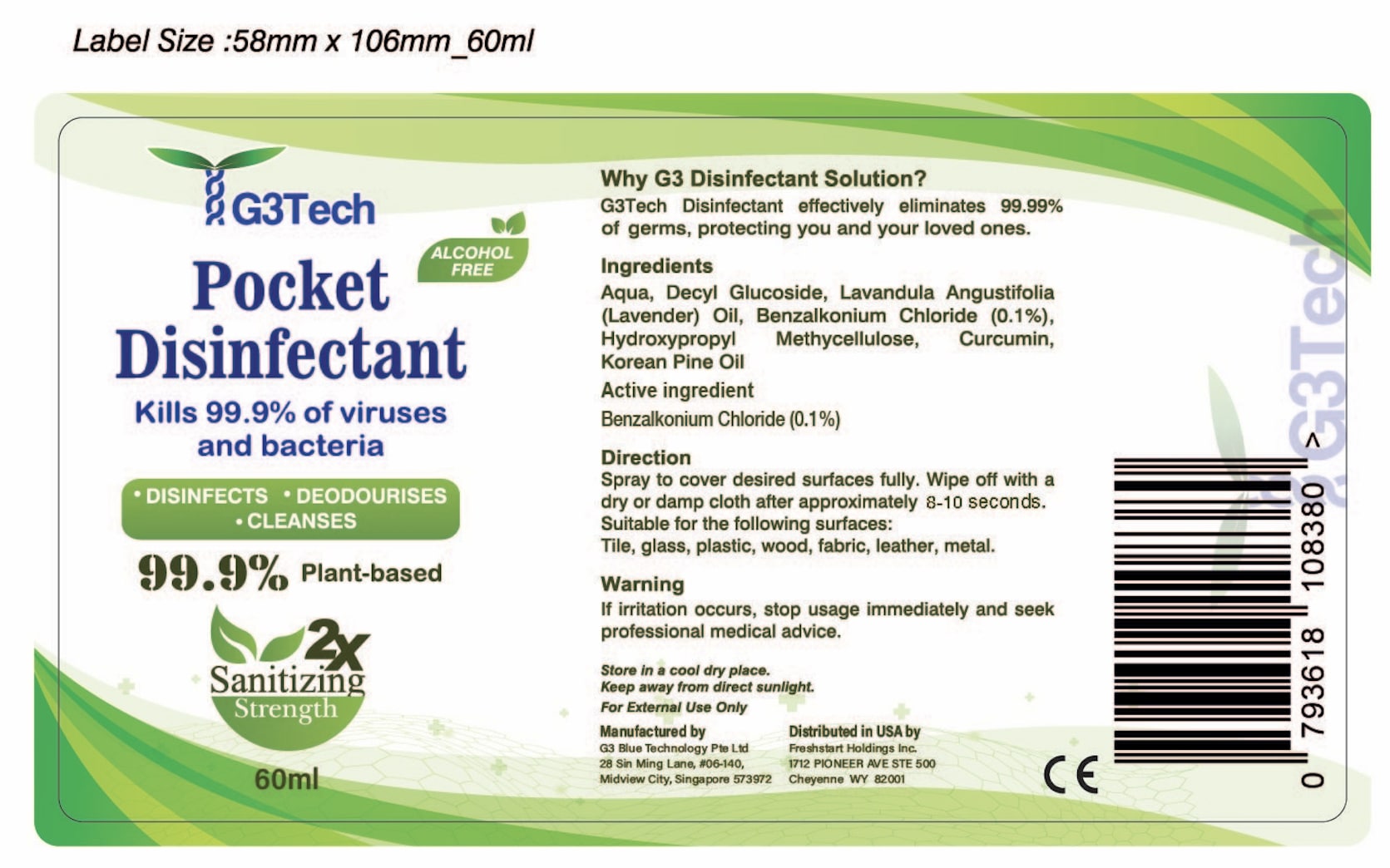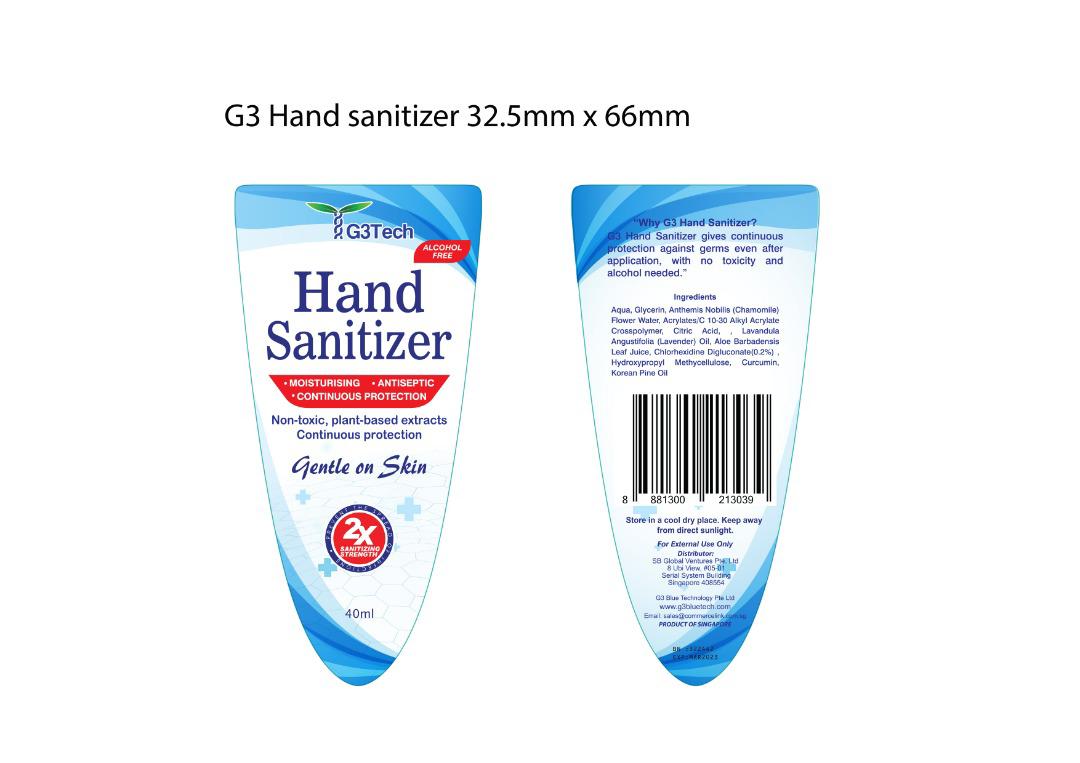 DRUG LABEL: G3Tech Disinfectant Coating
NDC: 80062-005 | Form: LIQUID
Manufacturer: G3 BLUE TECHNOLOGY PTE. LTD.
Category: otc | Type: HUMAN OTC DRUG LABEL
Date: 20201207

ACTIVE INGREDIENTS: BENZALKONIUM CHLORIDE 100 mg/1 mL
INACTIVE INGREDIENTS: WHITE PINE OIL; DECYL GLUCOSIDE; WATER; CURCUMIN; LAVENDER OIL; HYPROMELLOSE, UNSPECIFIED

Active Ingredient(s)

Benzalkonium Chloride 0.1% v/v. Purpose: Antiseptic

Purpose

Antiseptic, Topical

Use

Disinfectant spray to help reduce bacteria that help protect against infection on skin and surfaces.

Warnings

For external use only.

When using this product keep out of eyes, ears, and mouth. In case of contact with eyes, rinse eyes thoroughly with water.
Stop use and ask a doctor if irritation or rash occurs. These may be signs of a serious condition.
Keep out of reach of children. If swallowed, get medical help or contact a Poison Control Center right away.

Stop use and ask a doctor if irritation or rash occurs. These may be signs of a serious condition.

Keep out of reach of children. If swallowed, get medical help or contact a Poison Control Center right away.

Directions

- Spray to cover desired surfaces fully
- Wipe off with a dry or damp cloth after approximately 8-10 seconds

Suitable for the following surfaces:

Tile, glass, plastic, wood, fabric, leather, metal

Other information

- Store in a cool dry place
- Keep away from direct sunlight

Inactive ingredients

Aqua

Decyl Glucoside

Lavandula Angustifolia (Lavender) Oil

Hydroxypropyl Methycellulose

Curcumin

Korean Pine Oil

Package Label - Principal Display Panel

60 ml NDC: 80062-004-01